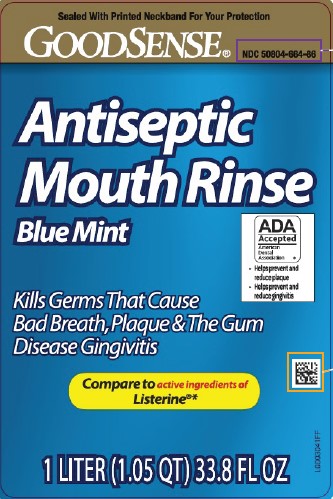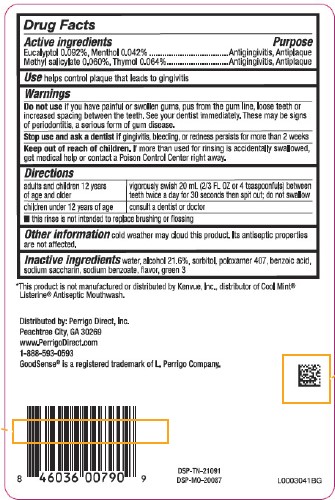 DRUG LABEL: Antispetic
NDC: 50804-664 | Form: MOUTHWASH
Manufacturer: Perrigo Direct, Inc 
Category: otc | Type: HUMAN OTC DRUG LABEL
Date: 20260219

ACTIVE INGREDIENTS: EUCALYPTOL 0.92 mg/1 mL; MENTHOL 0.42 mg/1 mL; METHYL SALICYLATE 0.6 mg/1 mL; THYMOL 0.64 mg/1 mL
INACTIVE INGREDIENTS: WATER; ALCOHOL; SORBITOL; POLOXAMER 407; BENZOIC ACID; SACCHARIN SODIUM; SODIUM BENZOATE; FD&C GREEN NO. 3

Good Sense 664.003/664AT rev 2-AU
Blue Mint Antiseptic Mouthrinse

Active ingredients

Eucalyptol 0.092%

Menthol 0.042%

Methyl salicylate 0.060%

Thymol 0.064%

Purpose

Antigingivitis, antiplaque

Use

helps control plaque that leads to gingivitis

Warnings

for this product

Do not use

if you have painful or swollen gums, pus from the gum line, loose teeth or increased spacing between the teeth. See your dentist immediately. These may be signs of periodontitis, a serious form of gum disease.

Stop use and ask a dentist if

gingivitis, bleeding, or redness persists for more than 2 weeks.

Keep out of reach of children.

If more than used for rinsing is accidentally swallowed, get medical help or contact a Poison Control Center right away.

Directions

adults and children 12 years of age and older - vigorously swish 20 mL (2/3 FL OZ or 4 teaspoonfuls) between teeth twice a day for 30 seconds then spit out; do not swallow

children under 12 years of age - consult a dentist or doctor

- this rinse is not intended to replace brushing or flossing

Other information

cold weather may cloud this product. Its antiseptic properties are not affected.

Inactive ingredients

water, alcohol 21.6%, sorbitol, poloxamer 407, benzoic acid, sodium saccharin, sodium benzoate, flavor, green 3

Disclaimer

*This product is not manufactured or distributed by Kenvue, Inc., distributor of Cool Mint®Listerine®Antiseptic Mouthwash.

ADVERSE REACTIONS SECTION

Distributed by: Perrigo Direct, Inc.

Peachtree City, GA 30269

www.PerrigoDirect.com

1-888-593-0593

Good Sense® is a registered trademark of L. Perrigo Company.

DSP-TN-21091

DSP-MO-20087

Principal Panel Display

Sealed With Printed Neckband For Your Protection

GOODSENSE®

NDC 50804-664-86

Antiseptic

Mouth Rinse

Blue Mint

ADA Accepted

American Dental Association

• Helps prevent and reduce plaque
• Helps prevent and reduce gingivitis

Kills Germs That Cause Bad Breath, Plaque & The gum Disease Gingivitis

Compare to active ingredients of Listerine®*

1 Liter (1.05 QT) 33.8 FL OZ